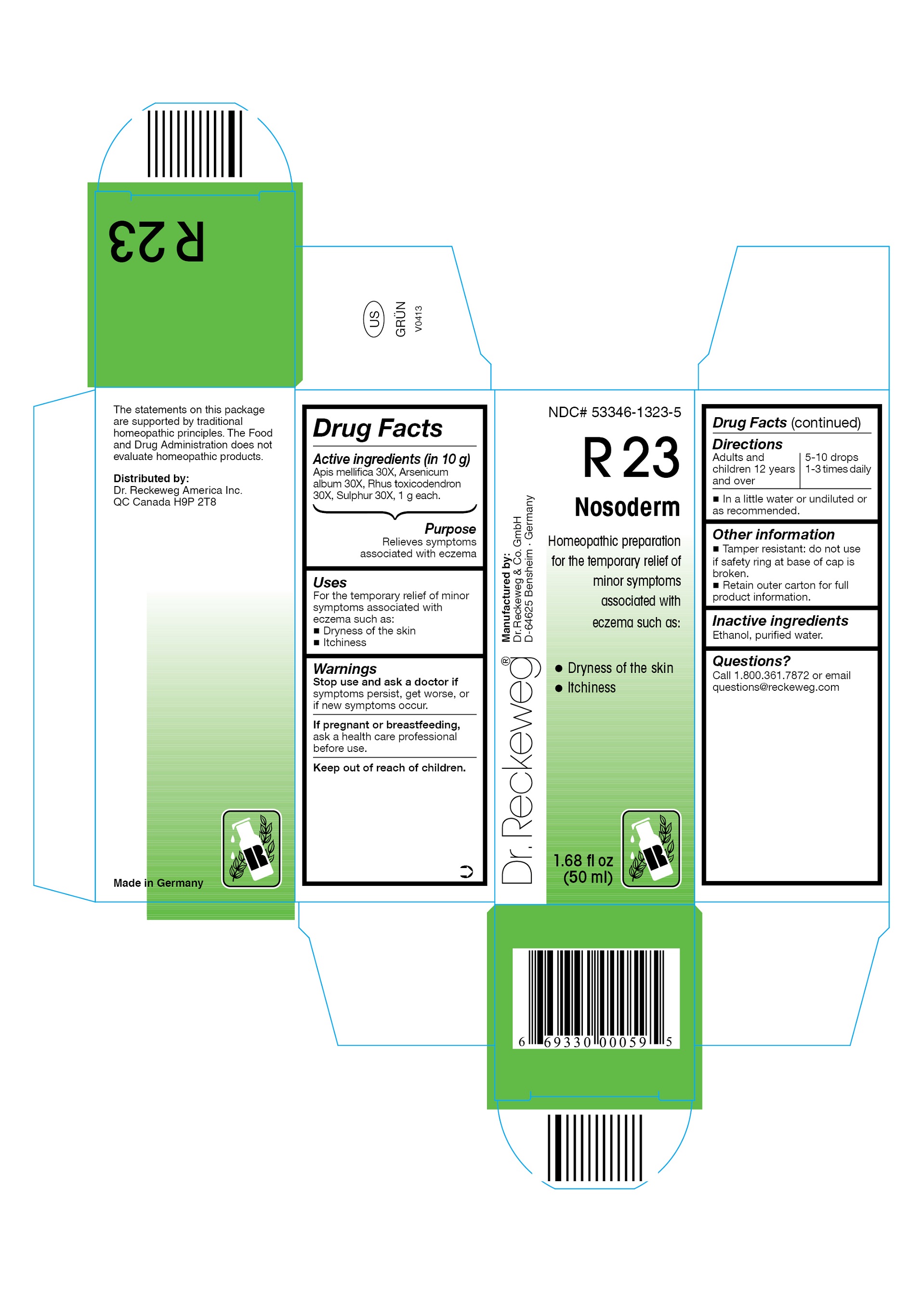 DRUG LABEL: DR. RECKEWEG R23 Nosoderm
NDC: 53346-1323 | Form: LIQUID
Manufacturer: PHARMAZEUTISCHE FABRIK DR. RECKEWEG & CO
Category: homeopathic | Type: HUMAN OTC DRUG LABEL
Date: 20130404

ACTIVE INGREDIENTS: APIS MELLIFERA 30 [hp_X]/50 mL; ARSENIC TRIOXIDE 30 [hp_X]/50 mL; TOXICODENDRON PUBESCENS LEAF 30 [hp_X]/50 mL; SULFUR 30 [hp_X]/50 mL
INACTIVE INGREDIENTS: ALCOHOL; WATER

DR. RECKEWEG R23 Nosoderm

Active ingredients

Apis mellifica 30X, Arsenicum album 30X, Rhus toxicodendron 30X, Sulphur 30X, 1 g each in 10 g.

Purpose

Relieves symptoms associated with eczema

Uses

For the temporary relief of minor symptoms associated with eczema such as:

- Dryness of the skin
- Itchiness

Warnings

Stop use and ask a doctor if symptoms persist, get worse, or if new symptoms occur.

PREGNANCY OR BREAST FEEDING

If pregnant or breastfeeding, ask a health care professional before use.

Keep out of reach of children.

Directions
Adults and children ≥ 12 years 5-10 drops 1-3 times daily in a little water or undiluted or as recommended.

Other information

- Tamper resistant: do not use if safety ring at base of cap is broken.
- Retain outer carton for full product instructions.

Inactive ingredients

Ethanol, purified water.

Questions?

Call 1-800-361-7872 or email questions@reckeweg.com

PACKAGE LABEL

NDC# 53346-1323-5

Dr. Reckeweg R23 Nosoderm

Homeopathic preparation for the temporary relief of minor symptoms associated with eczema such as:

- Dryness of the skin
- Itchiness

Manufactured by:

Dr. Reckeweg Co. GmbH

D-64625 Bensheim

Germany

1.68 fl oz
(50 ml)